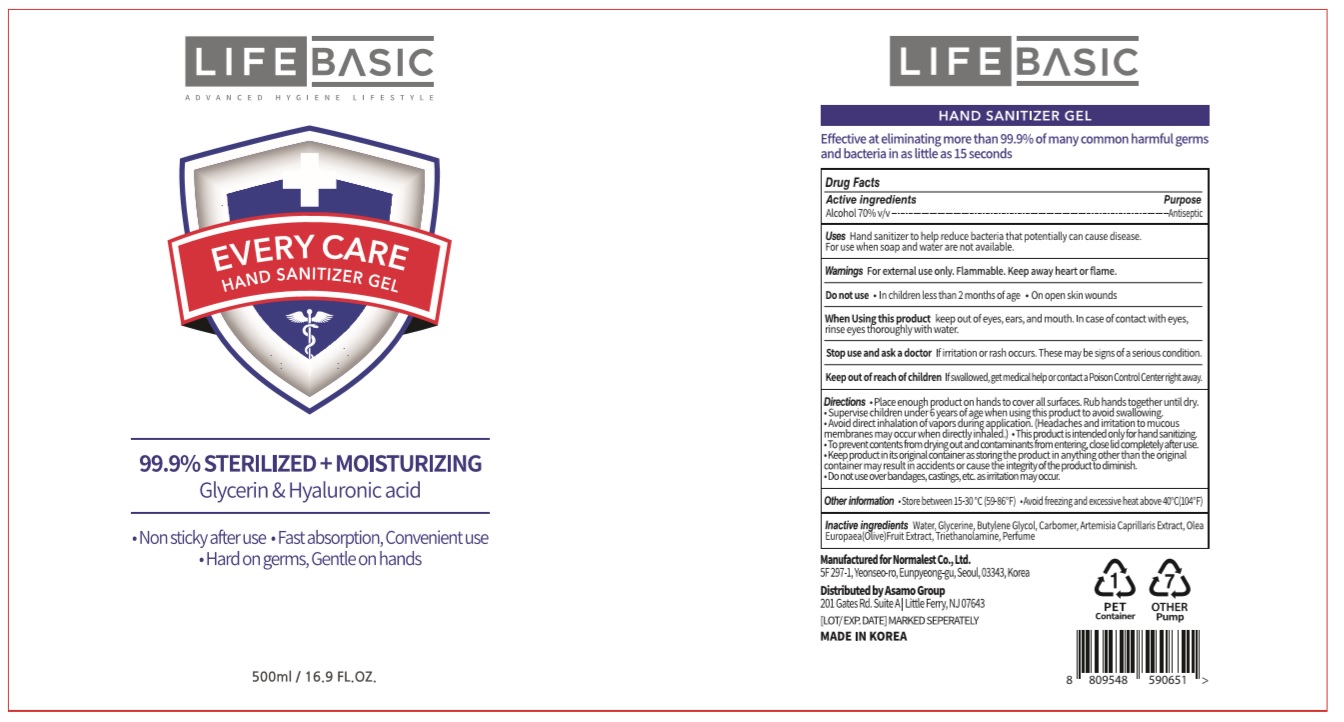 DRUG LABEL: LIFE BASIC EVERY CARE HAND SANITIZER Gel
NDC: 72284-1697 | Form: GEL
Manufacturer: Normalest Co., Ltd.
Category: otc | Type: HUMAN OTC DRUG LABEL
Date: 20200522

ACTIVE INGREDIENTS: ALCOHOL 350 mL/500 mL
INACTIVE INGREDIENTS: GLYCERIN; CARBOMER HOMOPOLYMER, UNSPECIFIED TYPE; WATER; BUTYLENE GLYCOL; ARTEMISIA CAPILLARIS FLOWER; TROLAMINE; BLACK OLIVE

LIFEBASIC ZERO CARE HAND SANITIZER Gel 500 ml : 72284-1697-1